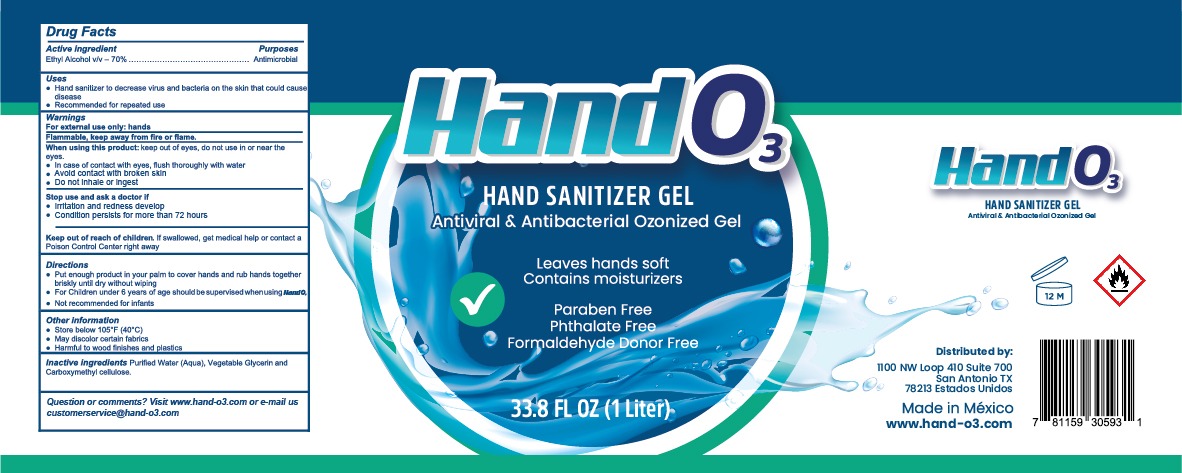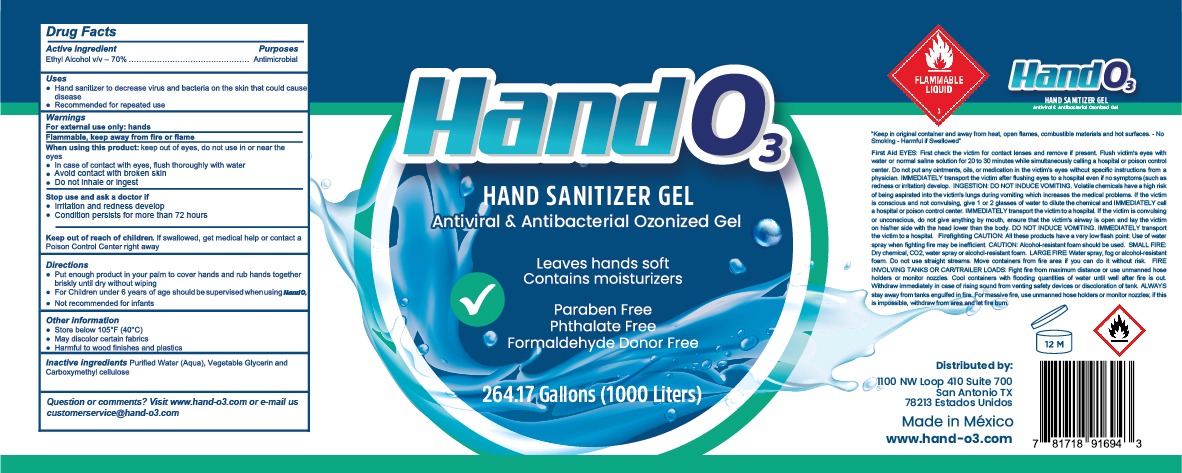 DRUG LABEL: HAND SANITIZER
NDC: 77210-0004 | Form: GEL
Manufacturer: EXPORTADORA IN & OUT S DE RL DE CV
Category: otc | Type: HUMAN OTC DRUG LABEL
Date: 20200521

ACTIVE INGREDIENTS: ALCOHOL 70 mL/100 mL
INACTIVE INGREDIENTS: GLYCERIN 3.17 mL/100 mL; WATER; CARBOXYMETHYLCELLULOSE 5 mL/100 mL

Active Ingredient

Ethyl Alchol v/v - 70%

Purposes

Antimicrobial

Uses

Hand sanitizer to derease virus and bacteria on the skin that could cause disease. For when water and soap are not available

Recommended for repeated use

Warnings

For external use only: hands

Flammable, keep away from fire or flame

When using this product

keep out eyes, ears and mouth. Do not use in or near the eyes.

In case of contact with eyes, flush thorougly with water

Avoid contact with broken skin

Do not inhale or ingest

When using this product

Keep out of eyes, ears and mouth. Do not use in or near the eyes.

In case of contact eyes, flush thorougly with water

Avoid contact with broken skin

Do not inhale or ingest

Stop use and ask a doctor if

Irritation and redness develop

Conditions persists for more than 72 hours

Keep out of reach of children

If swallowed, get medical help or contact a posion control center right away

Directions

-Put enough product in your palm to cover hands and rub hands together briskly until dry without wiping

-For Children under 6 years of age should be supervised when using hando3

-Not recommended for infants

Other information

Sotre below 105 F (40C)

May discolor certain fabrics

Harmful to wood finishes and plastics

Inactive ingredients

Purified water (Aqua), vegetable glycerin and carboxymethul cellulose

for the 1,000 lt label

Firefighting CAUTION: all these products have a very low flash point: use water spray when fighting fire may be inefficient: CAUTION: Alcohol-resistant foam should be used.SMALL FIRE: Dry Chemicals, co2, water spray or alcohol-resistant foam. LARGE FIRE: Water spray, fog or alcohol resistant foam. Do not use straight streams. Move containers from fire area if you can do it without risk. FIRE INVOLVING TANKS OR CAR/TRAILERS LOADS: Fight fire for maximun distance or use unmanned hose holders or monito nozzles: Cool containers with flooding quiantities of water until well after fire is out. Withdraw immediatly in case of rising sounf from venting safety devices or discoloration of thank. ALWAYS stay away from tanks engulfed in fire. For massive fire, use unmaned hose holders or monitor nozzles; if this is imposible. Withdraw from area and let the fire burn.

PACKAGE LABEL

hando3

hand sanitizer gel

antiviral & antibacterial ozonized gel

leaves hands soft

contains moisturizers

paraben free

phthalate free

formaldehyde donor free

33.8 fl oz (1 liter)

264.17 Gallons (1000 liters)